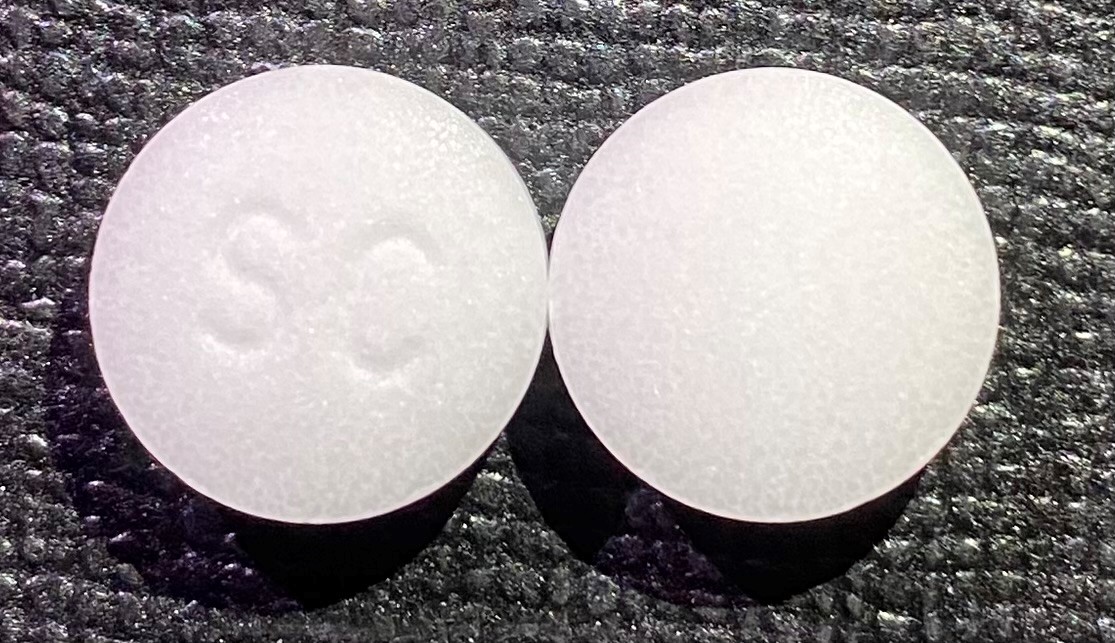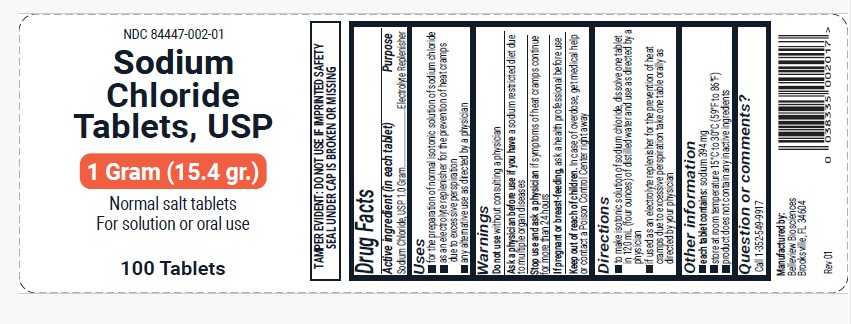 DRUG LABEL: Sodium Chloride
NDC: 84447-002 | Form: TABLET
Manufacturer: Belleview Bioscience LLC
Category: otc | Type: HUMAN OTC DRUG LABEL
Date: 20250324

ACTIVE INGREDIENTS: SODIUM CHLORIDE 1000 mg/1 1

DRUG FACTS

Active ingredient (in each tablet)
Sodium Chloride, USP 1 Gram

Purpose

Electrolyte Replenisher

USES

- for the preparation of normal isotonic solution of sodium chloride
- as an electrolyte replenisher for the prevention of heat cramps due to excessive perspiration
- any alternative use as directed by a physician

WARNINGS

Do not use without consulting a physician

Ask a physician before use if you have a sodium restricted diet due to multiple organ diseases

Stop use and ask a physician if symptoms of heat cramps continue for more than 24 hours

If pregnant or breast-feeding, ask a health professional before use

Overdose

In case of overdose, get medical help or contact a Poison Control Center right away.

DIRECTIONS

- to make isotonic solution of sodium chloride, dissolve one tablet in 120 mL (four ounces) of distilled water and use as directed by a physician
- if used as an electrolyte replenisher for the prevention of heat cramps due to excessive perspiration take one tablet orally as directed by your physician.

Other Information

- each tablet contains: sodium 394 mg
- store at room temperature 15ºC to 30ºC (59ºF to 86ºF)

Inactive Ingredients

- NONE

Questions or Comments

Call 1-352-549-9917

Manufactured By

Belleview Biosciences LLC

15431 Flight Path Dr

Brooksville, FL 34604

NDC 84447-002-01

Sodium Chloride Tablets, USP
1 Gram (15.4 gr.)
Normal salt tablets
For solution or oral use
100 Tablets